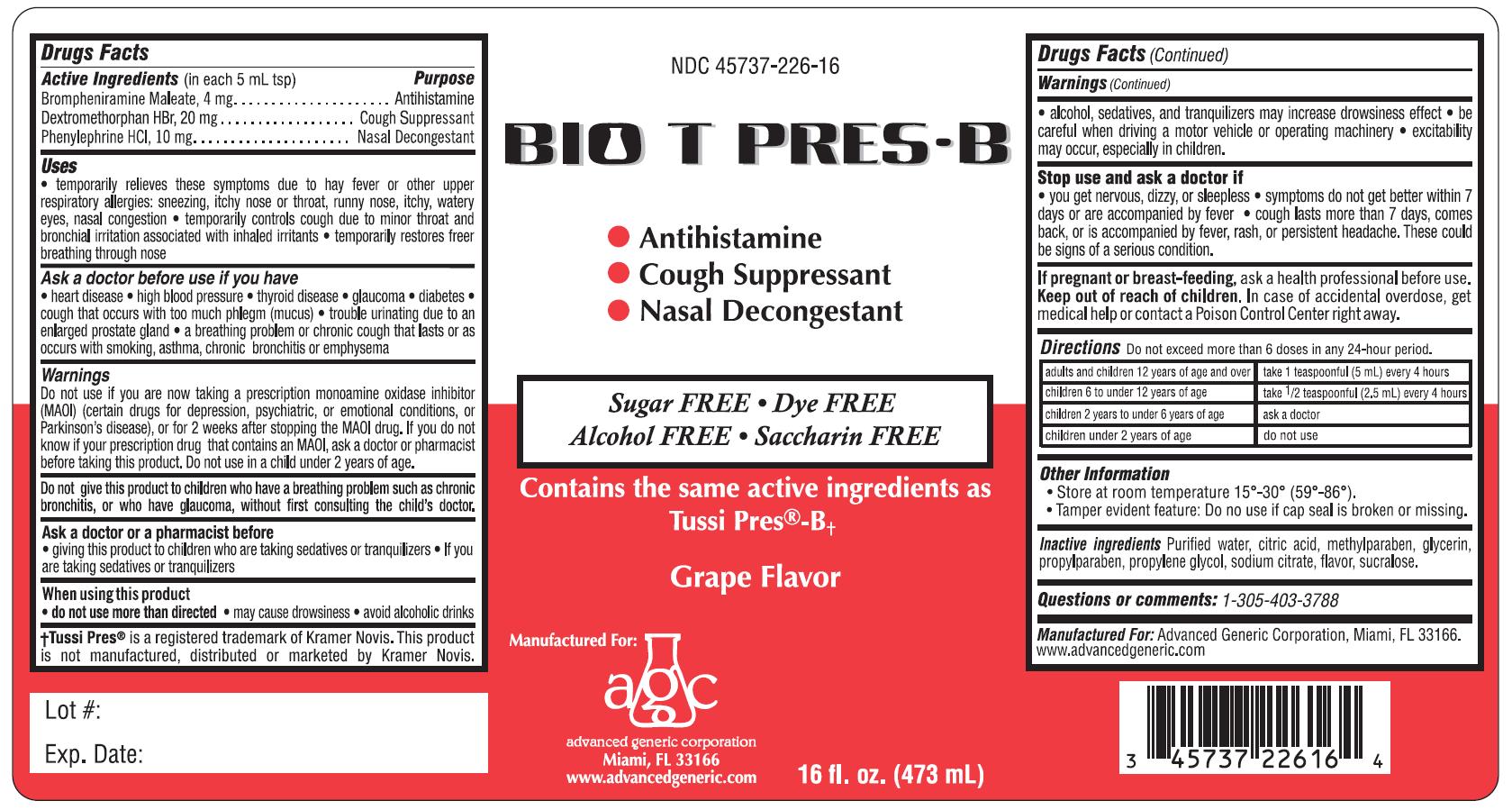 DRUG LABEL: Bio T Pres-B
NDC: 45737-226 | Form: LIQUID
Manufacturer: Advanced Generic Corporation
Category: otc | Type: HUMAN OTC DRUG LABEL
Date: 20121218

ACTIVE INGREDIENTS: BROMPHENIRAMINE MALEATE 4 mg/5 mL; DEXTROMETHORPHAN HYDROBROMIDE 20 mg/5 mL; PHENYLEPHRINE HYDROCHLORIDE 10 mg/5 mL
INACTIVE INGREDIENTS: WATER; CITRIC ACID MONOHYDRATE; METHYLPARABEN; GLYCERIN; PROPYLENE GLYCOL; PROPYLPARABEN; SODIUM CITRATE; SUCRALOSE

Drug Facts

Active Ingredients (in each 5 mL tsp) Purpose

Brompheniramine maleate 1 mg Antihistamine

Dextromethorphan HBr 5 mg Cough Suppressant

Phenylephrine HCl 2.5 mg Nasal Decongestant

Uses

- temporarily relieves symptoms due to hay fever or other upper respiratory allergies:
-
  - sneezing
  - itchy nose or throat
  - runny nose
  - itchy, water eyes
  - nasal congestion
- temporarily controls cough due to minor throat and bronchial irritation associated with inhaled irritants
- temporarily restores freer breathing through nose

Warnings

Do not use if you are now taking a prescription monoamine oxidase inhibitor (MAOI) (certain drugs for depression, psychiatric, or emotional conditions, or Parkinson's disease), or for 2 weeks after stopping the MAOI drug. If you do not know if your prescription drug contains an MAOI, ask a doctor or pharmacist before taking this product. Do not use on a child under 2 years of age.

Ask a doctor before use if you have

- heart disease
- high blood pressure
- thyroid disease
- glaucoma
- diabetes
- cough that occurs with too much phlegm (mucus)
- trouble urinating due to an enlarged prostate gland
- a breathing problem or chronic cough that lasts or as occurs with smoking, asthma, chronic bronchitis or emphysema

Ask a doctor or a pharmacist before

- giving this product to children who are taking sedatives or tranquilizers
- if you are taking sedatives or tranquilizers

DO NOT USE

Do not give this product to children who have a breathing problem such as chronic bronchitis, or who have glaucoma, without first consulting the child's doctor.

When using this product

- do not use more than directed
- may cause drowsiness
- avoid alcoholic drink
- alcohol, sedatives and tranquilizers may increase drowsiness effect
- be careful when driving a motor vehicle or operating machinery
- excitability may occur, especially in children

Stop use and ask a doctor if

- you get nervous, dizzy or sleeplessness
- symptoms do not get better within 7 days or are accompanied by fever
- cough lasts more than 7 days, comes back or is accompanied by fever, rash or persistent headache. These could be signs of a serious condition.

Keep out of reach of children.In case of accidental overdose, get medical help or contact a Poison Control Center right away.

PREGNANCY OR BREAST FEEDING

If pregnant or breast-feeding,ask a health professional before use.

DOSAGE AND ADMINISTRATION

Directions Do not exceed more than 6 doses in any 24-hour period.

adults and children 12 years of age and over | take 1 teaspoonfuls (5 mL) every 4 hours
children 6 to under 12 years of age | take 1/2 teaspoonfuls (2.5mL) every 4 hours
children 2 years to under 6 years of age | ask a doctor
children under 2 years of age | do not use

Other Information

- Store between 15-30 degrees C (59-89 degrees F)
- Tamper evident feature: Do not use if cap seal is broken or missing

Inactive Ingredients

Water, citric acid, methylparaben, glycerin, propylene glycol, propylparaben, sodium citrate, flavor, sucralose

Questions or comments: 1-305-403-3788

Advanced Generic Corporation, Miami, Fl 33166

www.advancedgeneric.com